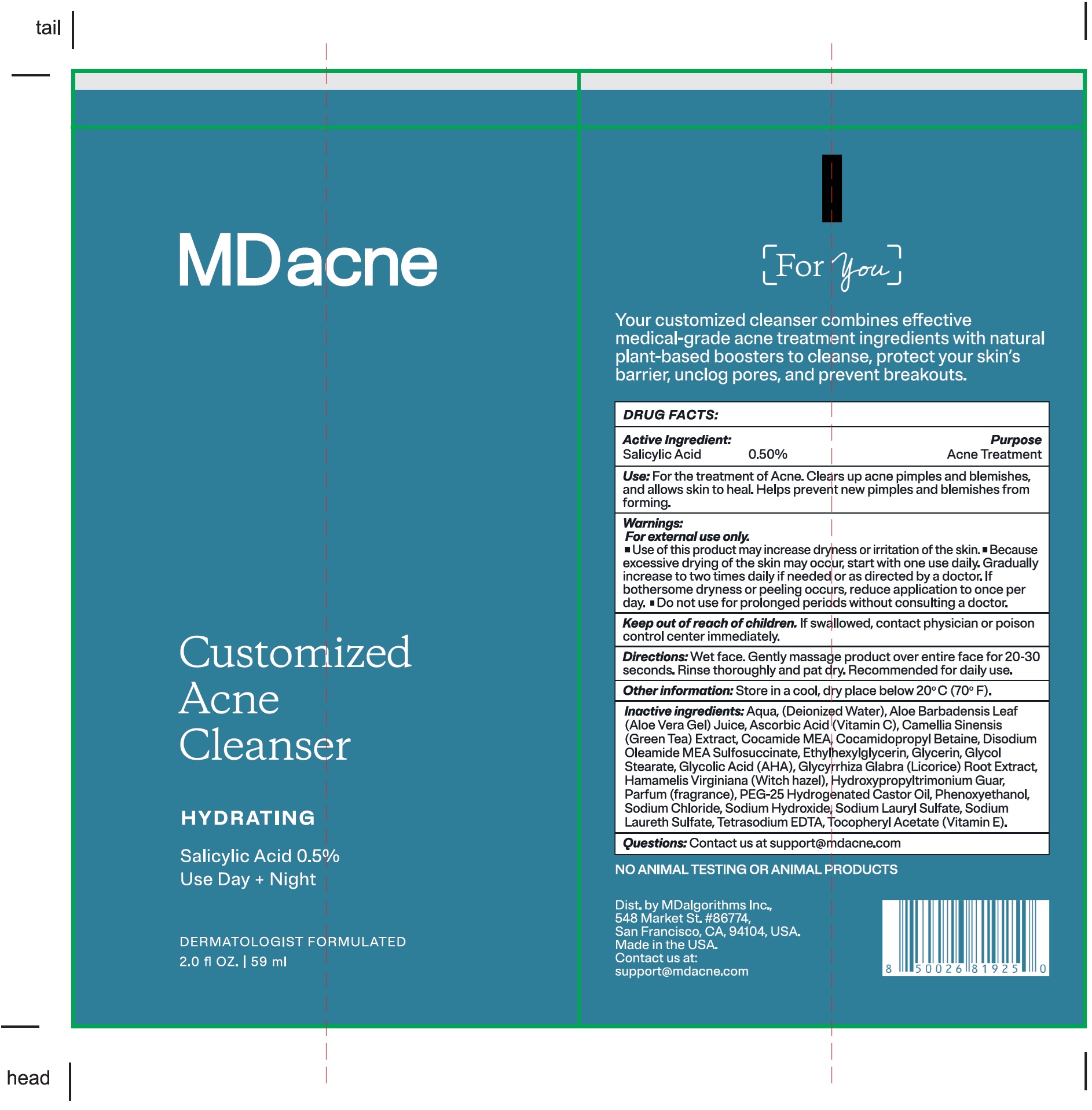 DRUG LABEL: MDacne Customized Acne Cleanser Hydrating Salicylic Acid
NDC: 71804-534 | Form: CREAM
Manufacturer: MDAlgorithms Inc
Category: otc | Type: HUMAN OTC DRUG LABEL
Date: 20240919

ACTIVE INGREDIENTS: SALICYLIC ACID 5 mg/1 mL
INACTIVE INGREDIENTS: WATER; ALOE VERA LEAF; ASCORBIC ACID; GREEN TEA LEAF; ETHYLHEXYLGLYCERIN; GLYCERIN; GLYCOL STEARATE; GLYCYRRHIZA GLABRA; WITCH HAZEL; PEG-25 HYDROGENATED CASTOR OIL; PHENOXYETHANOL; SODIUM CHLORIDE; SODIUM HYDROXIDE; SODIUM LAURYL SULFATE; SODIUM LAURETH SULFATE; EDETATE SODIUM; .ALPHA.-TOCOPHEROL ACETATE

MDacne Customized Acne Cleanser Hydrating Salicylic Acid 0.5%

Active Ingredient:

Salicylic Acid 0.50%

Purpose

Acne Treatment

Use:

For the treatment of Acne. Clears up acne pimples and blemishes, and allows skin to heal. Helps prevent new pimples and blemishes from forming.

Warnings:

For external use only.

- Use of this product may increase dryness or irritation of the skin.
- Because excessive drying of the skin may occur, start with one use daily. Gradually increase to two times daily if needed or as directed by a doctor. If bothersome dryness or peeling occurs, reduce application to once per day.

• Do not use

for prolonged periods without consulting a doctor.

Keep out of reach of children.

If swallowed, contact physician or poison control center immediately.

Directions:

Wet face. Gently massage product over entire face for 20-30 seconds. Rinse thoroughly and pat dry. Recommended for daily use.

Other information:

Store in a cool, dry place below 20ºC (70ºF).

Inactive Ingredients:

Aqua (Deionized Water), Aloe Barbadensis Leaf (Aloe Vera gel) Juice, Ascorbic Acid (Vitamin C), Camellia Sinensis (Green Tea) Extract, Cocamide MEA Cocamidopropyl Betaine, Disodium Oleamide MEA Sulfosuccinate, Ethylhexylglycerin, Glycerin, Glycol Stearate, Glycolic Acid (AHA), Glycyrrhiza Glabra (Licorice) Root Extract, Hamamelis Virginiana (Witch hazel), Hydroxypropyltrimonium Guar, Parfum (fragrance), PEG-25 Hydrogenated Castor Oil, Phenoxyethanol, Sodium Chloride, Sodium Hydroxide, Sodium Lauryl Sulfate, Sodium Laureth Sulfate, Tetrasodium EDTA, Tocopheryl Acetate (Vitamin E).

Questions:

Contact us at support@mdacne.com